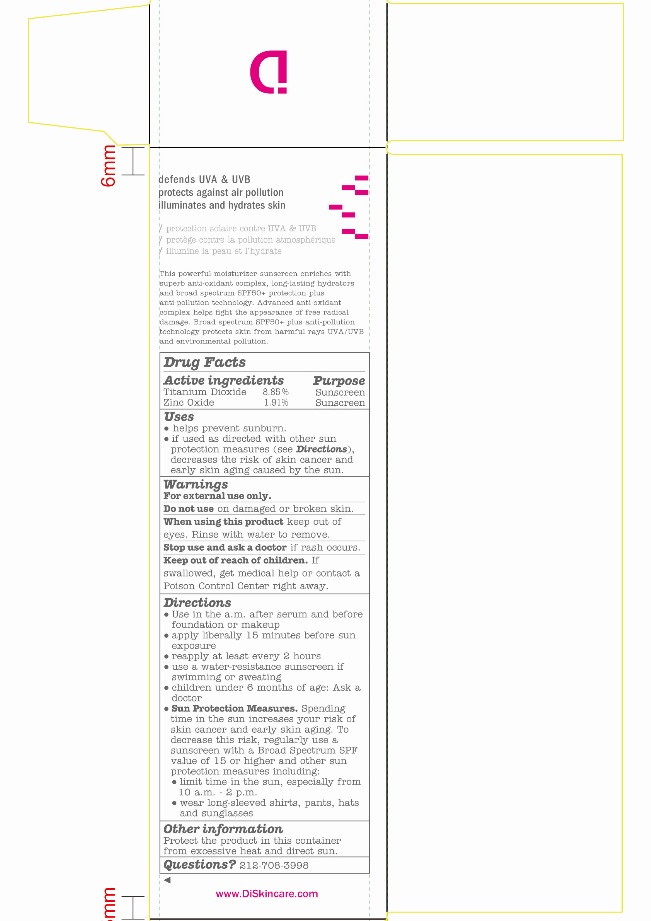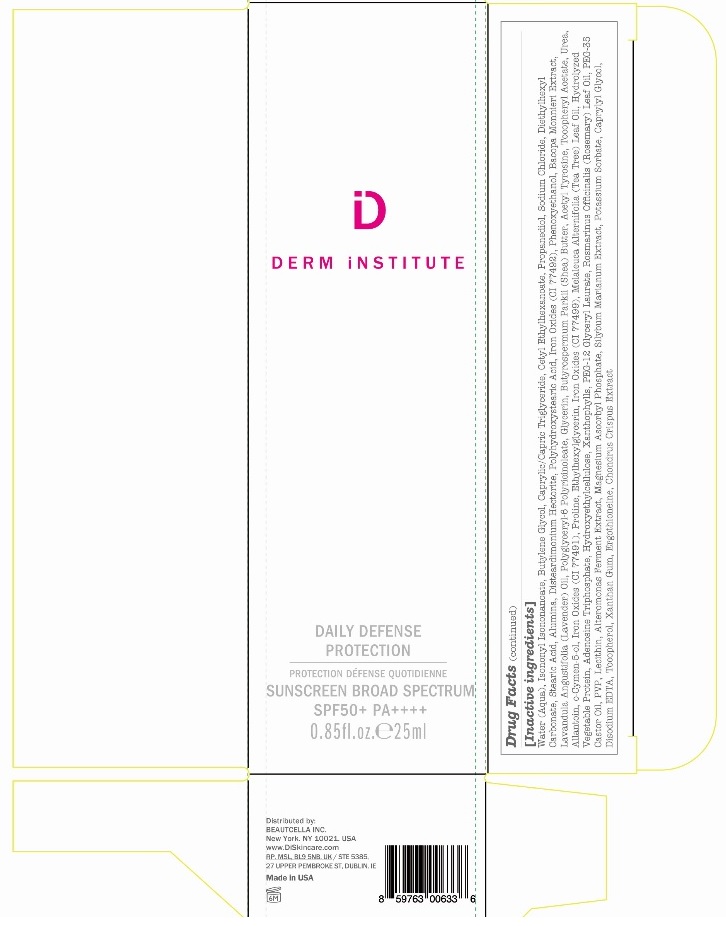 DRUG LABEL: Derm Institute Daily Defense Protection Sunscreen Broad Spectrum SPF50
NDC: 81521-001 | Form: LOTION
Manufacturer: Beautcella Inc.
Category: otc | Type: HUMAN OTC DRUG LABEL
Date: 20241206

ACTIVE INGREDIENTS: TITANIUM DIOXIDE 88.5 mg/1 mL; ZINC OXIDE 19.1 mg/1 mL
INACTIVE INGREDIENTS: CAPRYLYL GLYCOL; TOCOPHEROL; ADENOSINE TRIPHOSPHATE; PROLINE; ETHYLHEXYLGLYCERIN; TEA TREE OIL; HYDROXYETHYL CELLULOSE, UNSPECIFIED; POLYOXYL 35 CASTOR OIL; XANTHAN GUM; UREA; PHENOXYETHANOL; FERRIC OXIDE YELLOW; ACETYL L-TYROSINE; MEDIUM-CHAIN TRIGLYCERIDES; DIETHYLHEXYL CARBONATE; STEARIC ACID; SODIUM CHLORIDE; POLYHYDROXYSTEARIC ACID (2300 MW); FERROSOFERRIC OXIDE; CETYL ETHYLHEXANOATE; WATER; ISONONYL ISONONANOATE; O-CYMEN-5-OL; FERRIC OXIDE RED; CHONDRUS CRISPUS CARRAGEENAN; LUTEIN; ROSEMARY OIL; BACOPA MONNIERI WHOLE; SHEA BUTTER; .ALPHA.-TOCOPHEROL ACETATE; ALLANTOIN; BUTYLENE GLYCOL; PROPANEDIOL; ALUMINUM OXIDE; DISTEARDIMONIUM HECTORITE; EDETATE DISODIUM; POVIDONE; ERGOTHIONEINE; MAGNESIUM ASCORBYL PHOSPHATE; LAVENDER OIL; POLYGLYCERYL-6 POLYRICINOLEATE; GLYCERIN; PEG-12 GLYCERYL LAURATE; LECITHIN, SOYBEAN; MILK THISTLE; POTASSIUM SORBATE

Derm Institute Daily Defense Protection Sunscreen Broad Spectrum SPF50+

Active ingredients

Titanium Dioxide 8.85%

Zinc Oxide 1.91%

Purpose

Sunscreen

Uses

- helps prevent sunburn.
- if used as directed with other sun protection measures (see Directions), decreases the risk of skin cancer and early skin aging caused by the sun.

Warnings

For external use only.

Do not use

on damaged or broken skin.

When using this product

keep out of eyes. Rinse with water to remove.

Stop use and ask a doctor

if rash occurs.

Keep out of reach of children.

If swallowed, get medical help or contact a Poison Control Center right away.

Directions

- Use in the a.m. after serum and before foundation or makeup
- apply liberally 15 minutes before sun exposure
- reapply at least every 2 hours
- use a water-resistant sunscreen if swimming or sweating
- children under 6 months of age: Ask a doctor
- Sun Protection Measures. Spending time in the sun increases your risk of skin cancer and early skin aging. To decrease this risk, regularly use a sunscreen with a Broad Spectrum SPF value of 15 or higher and other sun protection measures including:
- limit time in the sun, especially from 10 a.m. - 2 p.m.
- wear long-sleeved shirts, pants, hats and sunglasses

Other information

Protect the product in this container from excessive heat and direct sun.

Questions?

212-708-3998

Inactive ingredients

Water (Aqua), Isononyl Isononanoate, Butylene Glycol, Caprylic/Capric Triglyceride, Cetyl Ethylhexanoate, Propanediol, Sodium Chloride, Diethylhexyl Carmonate, Stearic Acid, Alumina, Disteardimonium Hectorite, Polyhydroxystearic Acid, Iron Oxides (CI 77492), Phenoxyethanol, Bacopa Monnieri Extract, Lavandula Angustifolia (Lavender) Oil, Polyglyceryl-6 Polyricinoleate, Glycerin, Butyrospermum Parkii (Shea) Butter, Acetyl Tyrosine, Tocopheryl Acetate, Urea, Allantoin, o-Cymen-5-ol, Iron Oxides (CI 77491), Proline, Ethylhexylglycerin, Iron Oxides (CI 77499), Melaleuca Alternifolia (Tea Tree) Leaf Oil, Hydrolyzed Vegetable Protein, Adenosine Triphosphate, Hydroxyethylcellulose, Xanthophylls, PEG-12 Glyceryl Laurate, Rosmarinus Officininalis (Rosemary) Leaf Oil, PEG-35 Castor Oil, PVP, Lecithin, Alteromonas Ferment Extract, Magnesium Ascorbyl Phosphate, Silybum Marianum Extract, Potassium Sorbate, Caprylyl Glycol, Disodium EDTA, Tocopherol, Xanthan Gum, Ergothioneine, Chondrus Crispus Extract

Company Information

Distributed by: Beautcella Inc. New York, NY 10021 USA

www.DiSkincare.com